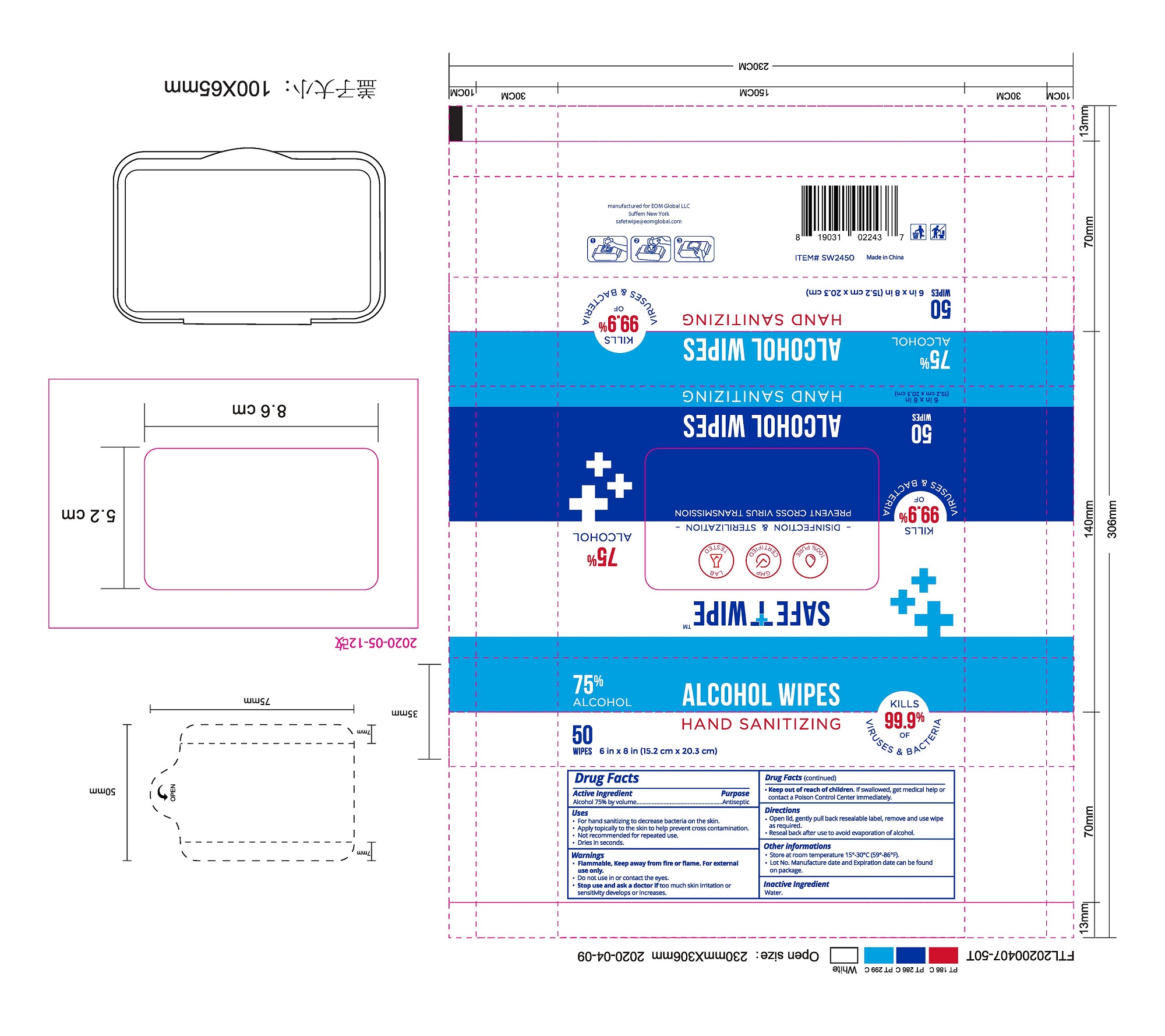 DRUG LABEL: Hand Sanitizing Alcohol Wipes
NDC: 80399-001 | Form: CLOTH
Manufacturer: Jinhua Hongyuan Daily Chemicals Technology Co., Ltd.
Category: otc | Type: HUMAN OTC DRUG LABEL
Date: 20200831

ACTIVE INGREDIENTS: ALCOHOL 75 mL/100 mL
INACTIVE INGREDIENTS: WATER

80399-001 hand sanitizing alcohol wipes 75% alcohol

Active Ingredient(s)

Alcohol 75% by volume

Purpose

Antiseptic

Use

For hand sanitizing to decrease bacteria on the skin.
Apply topically to the skin to help prevent cross contamination.
Not recommended for repeated use.
Dries in seconds.

Warnings

.Flammable, Keep away from fire or flame. For external
use only.
. Do not use in or contact the eyes.
. Stop use and ask a doctor if too much skin irritation or sensitivity develops or increases.

. Keep out of reach of children. If swallowed,
get medical help or contact a Poison control Center immediately

Directions

Open lid, gently pull back resealable label, remove and use wipe
Reseal back after use to avoid evaporation of alcohol.

Store at room temperature 15-30°C(59°-86°F).
Lot No. Manufacture date and Expiration date can be found on a package.

Inactive ingredients

Water